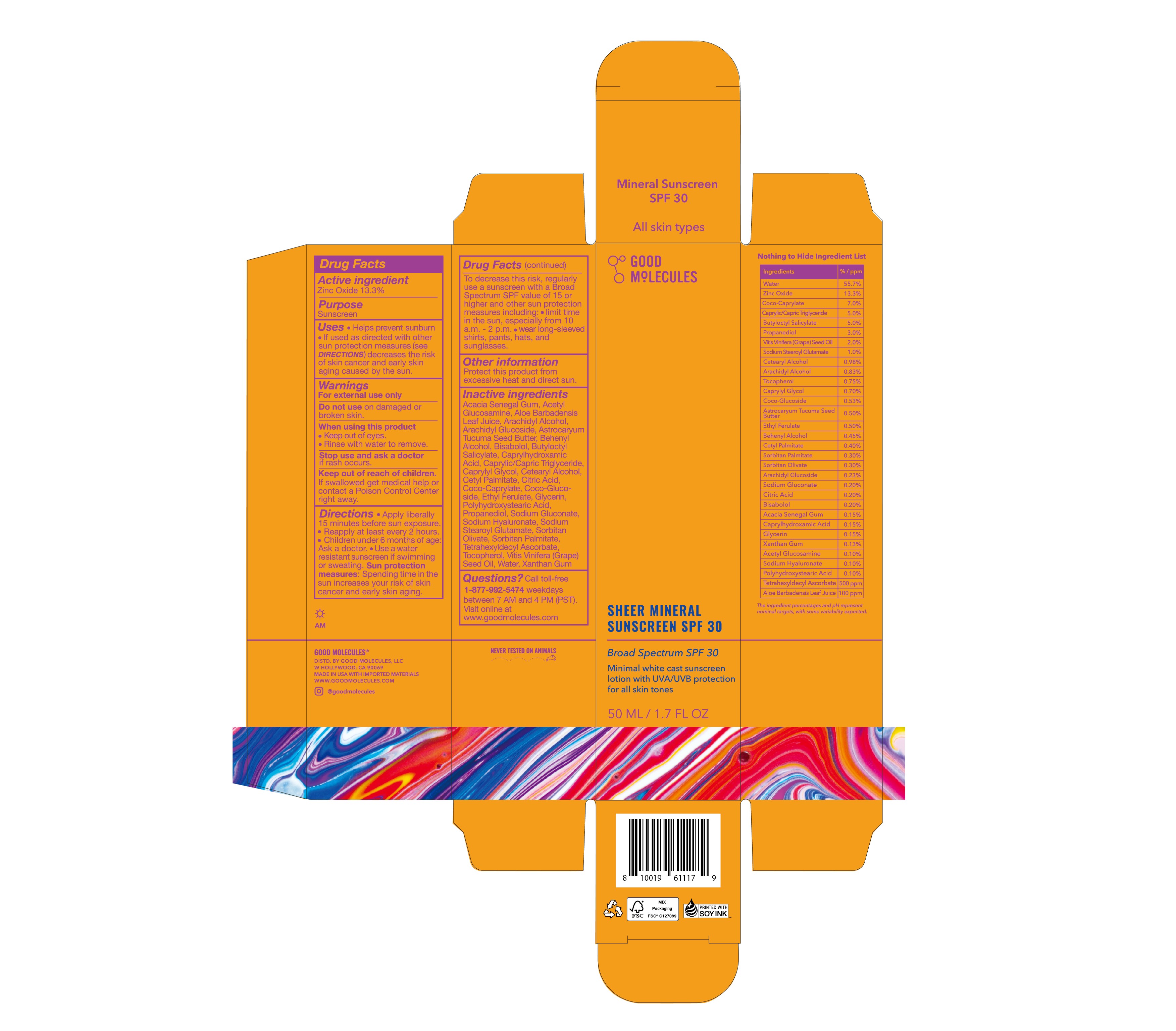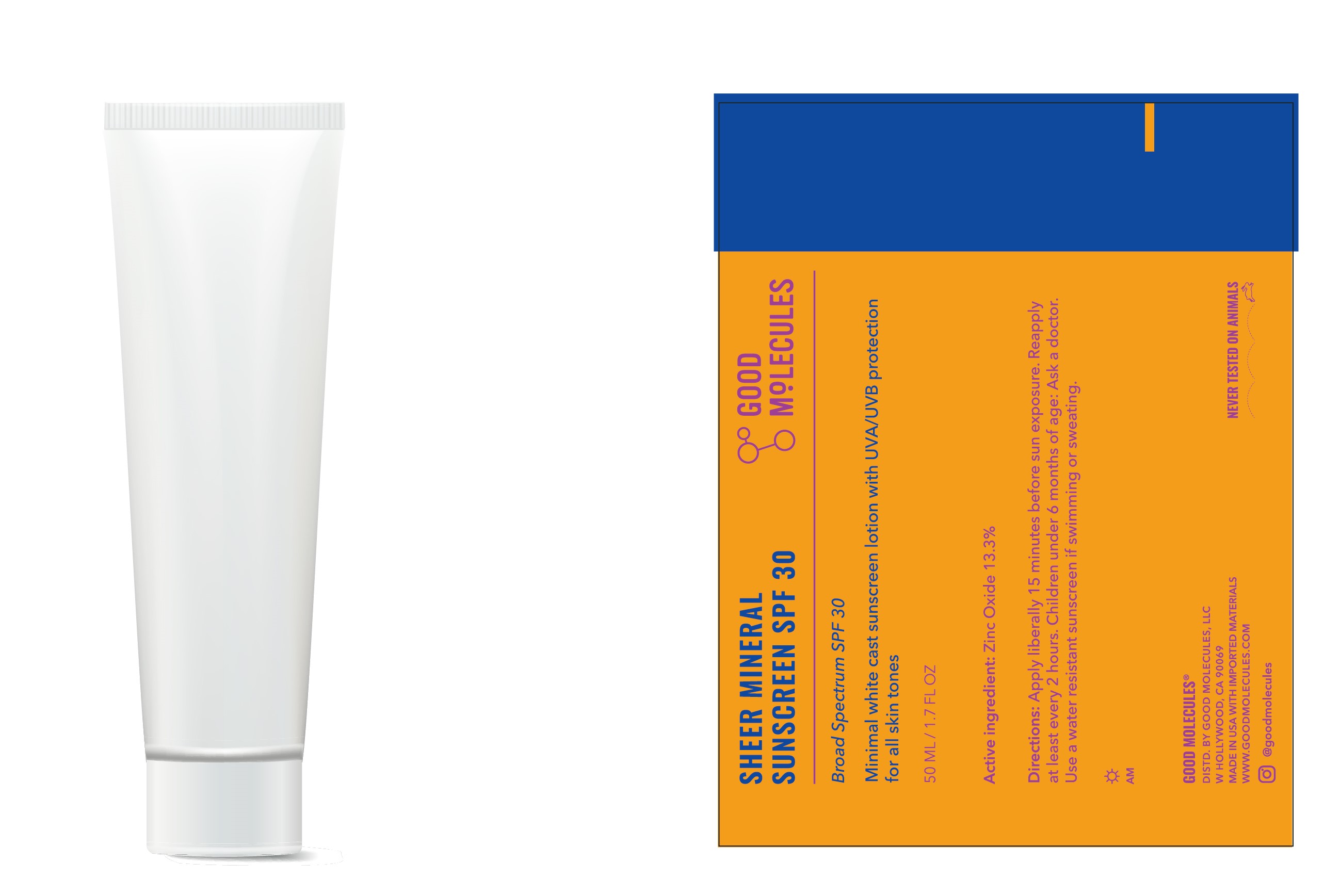 DRUG LABEL: Good Molecules Sheer Mineral Sunscreen SPF 30
NDC: 82730-101 | Form: LOTION
Manufacturer: Good Molecules, LLC
Category: otc | Type: HUMAN OTC DRUG LABEL
Date: 20240402

ACTIVE INGREDIENTS: ZINC OXIDE 13.3 g/100 mL
INACTIVE INGREDIENTS: CITRIC ACID MONOHYDRATE; GLYCERIN; COCO GLUCOSIDE; ALOE VERA LEAF; WATER; COCO-CAPRYLATE; HYALURONATE SODIUM; TETRAHEXYLDECYL ASCORBATE; CAPRYLYL GLYCOL; CETYL PALMITATE; ARACHIDYL ALCOHOL; POLYHYDROXYSTEARIC ACID (2300 MW); SODIUM GLUCONATE; CETOSTEARYL ALCOHOL; ARACHIDYL GLUCOSIDE; DOCOSANOL; SODIUM STEAROYL GLUTAMATE; SORBITAN OLIVATE; SORBITAN MONOPALMITATE; XANTHAN GUM; ASTROCARYUM ACULEATUM SEED OIL; LEVOMENOL; MEDIUM-CHAIN TRIGLYCERIDES; ETHYL FERULATE; TOCOPHEROL; CAPRYLHYDROXAMIC ACID; BUTYLOCTYL SALICYLATE; PROPANEDIOL; GRAPE SEED OIL; ACACIA; N-ACETYLGLUCOSAMINE

Good Molecules Sheer Mineral Sunscreen SPF 30

ACTIVE INGREDIENT

Zinc Oxide - 13.3%

PURPOSE

Sunscreen

Uses

• Helps prevent sunburn
• If used as directed with other sun protection measures (see Directions), decreases the risk of skin cancer and early skin aging caused by the sun.

WARNINGS

• For external use only.
• Do not useon damaged or broken skin.
• When using this productkeep out of eyes. Rinse with water to remove.
• Stop use and ask a doctorif rash occurs.

• Keep out of reach of children.If swallowed, get medical help or contact a Poison Control Center right away.

Directions

- Apply liberally 15 minutes before sun exposure.
- Reapply at least every 2 hours.
- Children under 6 months of age: Ask a doctor.
- Use a water resistant sunscreen if swimming or sweating.
  - Sun Protection Measure:Spending time in the sun increases your risk of skin cancer and early skin aging. To decrease this risk, regularly use a sunscreen with a Broad Spectrum SPF value of 15 or higher and other sun protection measures including:
    • Limit time in the sun, especially from 10 a.m. to 2 p.m.
    • Wear long-sleeved shirts, pants, hats, and sun glasses.

INACTIVE INGREDIENT

Acacia Senegal Gum
Acetyl Glucosamine
Aloe Barbadensis Leaf Juice
Arachidyl Alcohol
Arachidyl Glucoside
Astrocaryum Tucuma Seed Butter
Behenyl Alcohol
Bisabolol
Butyloctyl Salicylate
Caprylhydroxamic Acid
Caprylic/Capric Triglyceride
Caprylyl Glycol
Cetearyl Alcohol
Cetyl Palmitate
Citric Acid
Coco-Caprylate
Coco-Glucoside
Ethyl Ferulate
Glycerin
Polyhydroxystearic Acid
Propanediol
Sodium Gluconate
Sodium Hyaluronate
Sodium Stearoyl Glutamate
Sorbitan Olivate
Sorbitan Palmitate
Tetrahexyldecyl Ascorbate
Tocopherol
Vitis Vinifera (Grape) Seed Oil
Water
Xanthan Gum

Other Information

Protect this product from excessive heat and direct sun.

QUESTIONS

Call toll-free 1-877-992-5474 weekdays between 7 AM and 4 PM (PST). Visit online at www.goodmolecules.com